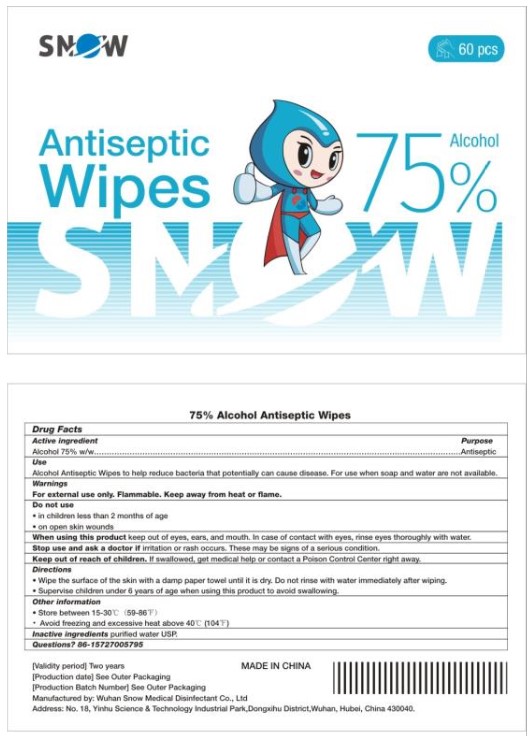 DRUG LABEL: 75% Alcohol Antiseptic Wipes
NDC: 80334-0630 | Form: CLOTH
Manufacturer: Wuhan Snow Medical Disinfectant Co., Ltd
Category: otc | Type: HUMAN OTC DRUG LABEL
Date: 20231227

ACTIVE INGREDIENTS: ALCOHOL 75 g/100 g
INACTIVE INGREDIENTS: WATER

Active Ingredient(s)

Alcohol 75% w/w. Purpose: Antiseptic

Purpose

Antiseptic, Hand Sanitizer

Use

Alcohol Antiseptic Wipes to help reduce bacteria that potentially can cause disease. For use when soap and water are not available.

Warnings

For external use only. Flammable. Keep away from heat or flame

Do not use

- in children less than 2 months of age
- on open skin wounds

When using this product keep out of eyes, ears, and mouth. In case of contact with eyes, rinse eyes thoroughly with water.
Stop use and ask a doctor if irritation or rash occurs. These may be signs of a serious condition.
Keep out of reach of children. If swallowed, get medical help or contact a Poison Control Center right away.

Stop use and ask a doctor if irritation or rash occurs. These may be signs of a serious condition.

Keep out of reach of children. If swallowed, get medical help or contact a Poison Control Center right away.

Directions

- Wipe the surface of the skin with a damp paper towel until it is dry. Do not rinse with water immediately after wiping.
- Supervise children under 6 years of age when using this product to avoid swallowing.

Other information

- Store between 15-30C (59-86F)
- Avoid freezing and excessive heat above 40C (104F)

Inactive ingredients

purified water USP.

Package Label - Principal Display Panel

60 Wipes NDC: 80334-0630-1